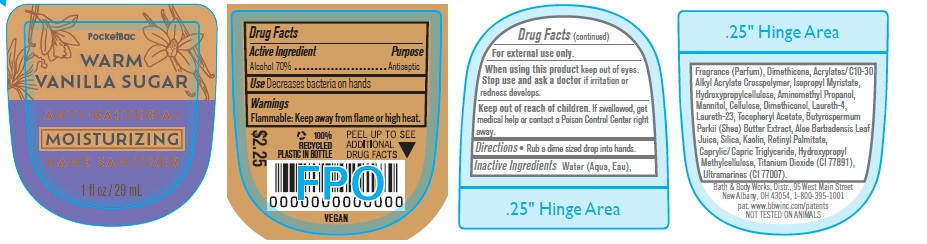 DRUG LABEL: Anti Bacterial Moisturizing Hand Gel
NDC: 62670-6676 | Form: GEL
Manufacturer: Bath & Body Works, Inc.
Category: otc | Type: HUMAN OTC DRUG LABEL
Date: 20260204

ACTIVE INGREDIENTS: ALCOHOL 70 mL/100 mL
INACTIVE INGREDIENTS: WATER

ABHG Warm Vanilla Sugar

Active Ingredient

Alcohol 70%

Purpose

Antiseptic

Use

Decreases bacteria on hands.

Warnings

Flammable: Keep away from flame or high heat.

WARNINGS

For external use only.

When using this product keep out of eyes. Stop use and ask a doctor if irritation or redness develops.

Keep out of reach of children. If swallowed, get medical help or contact a Poison Control Center right away.

Directions

Rub a dime sized drop into hands.

INACTIVE INGREDIENT

Water (Aqua, Eau), Fragrance (Parfum), Dimethicone, Acrylates/C10-30 Alkyl Acrylate Crosspolymer, Isopropyl Myristate, Hydroxypropylcellulose, Aminomethyl Propanol, Mannitol, Cellulose, Dimethiconol, Laureth-4, Laureth-23, Tocopheryl Acetate, Butyrospermum Parkii (Shea) Butter Extract, Aloe Barbadensis Leaf Juice, Silica, Kaolin, Retinyl Palmitate, Caprylic/Capric Triglyceride, Hydroxypropyl Methylcellulose, Titanium Dioxide (CI 77891), Ultramarines (CI 77007).

Bath & Body Works, Distr., 95 West Main Street
New Albany, OH 43054, 1-800-395-1001
pat. www.bbwinc.com/patents